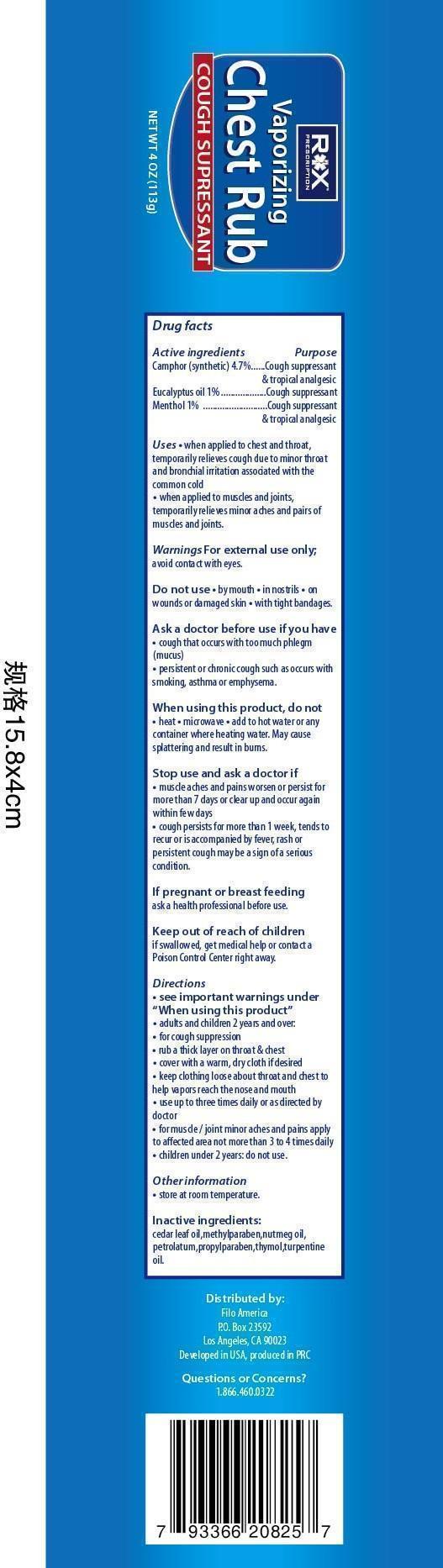 DRUG LABEL: Vaporizing Chest Rub
NDC: 50438-502 | Form: OINTMENT
Manufacturer: Filo America
Category: otc | Type: HUMAN OTC DRUG LABEL
Date: 20150505

ACTIVE INGREDIENTS: Camphor (Synthetic) 4.7 g/100 g; Eucalyptus Oil 1 g/100 g; Menthol 1 g/100 g
INACTIVE INGREDIENTS: Nutmeg Oil 0.6 g/100 g; TURPENTINE OIL; Petrolatum; propylparaben; THYMOL

VAPORIZING
CHEST RUB

Drug Facts

ACTIVE INGREDIENT

Active ingredients | Purpose
Camphor 4.7% | Cough suppressant/topical analgesic
Eucalyptus oil 1% | Cough suppressant
Menthol, natural 1% | Cough suppressant / topical analgesic

Use

when applied to chest and throat

- temporarily relieves cough due to minor throat and bronchial irritation associated with a cold

when applied to muscles and joints

- temporarily relieves minor aches and pains of muscles and joints

Warnings

For external use only; avoid contact with eyes.

Ask a doctor before use if you have

- cough that occurs with too much phlegm (mucus)
- persistent or chronic cough such as occurs with smoking, asthma, or emphysema

When using this product

- do not heat
- do not microwave
- do not add to hot water or any container where heating water. May cause splattering and result in burns.
- do not take by mouth or place in nostrils

Stop use and ask a doctor if

- cough persists for more than 1 week, tends to recur or is accompanied by fever, rash, or persistent cough may be a sign of a serious condition.
- muscle aches and pains worsen, persist for more than 7 days, or clear up occur again within a few days.

Keep out of reach of children. If swallowed, get medical help or contact a Poison Control Center right away.

Directions

- see important warnings under "When using this product"
- adults and children 2 year and over.

for cough suppression

- rub a thick layer on the throat and chest
- cover with a warm, dry cloth if desired
- keep clothing loose about throat and chest to help vapors reach the nose and mouth
- use up to 3 times daily, or as directed by a doctor

for muscle/joint minor aches and pains apply

- to affected area not more than 3-4 times daily
- children under 2 yeas : ask a doctor

other information

- store at room temperature

if pregnant or breast feeding

- ask a health professional before use

Inactive ingredients

Cedar leaf oil, methylparaben, Nutmeg oil, petrolatum, Turpentine oil, Thymol, propylparaben

PRINCIPAL DISPLAY PANEL - 100g Jar Label

VAPORIZING
CHEST RUB

4 oz (113g)